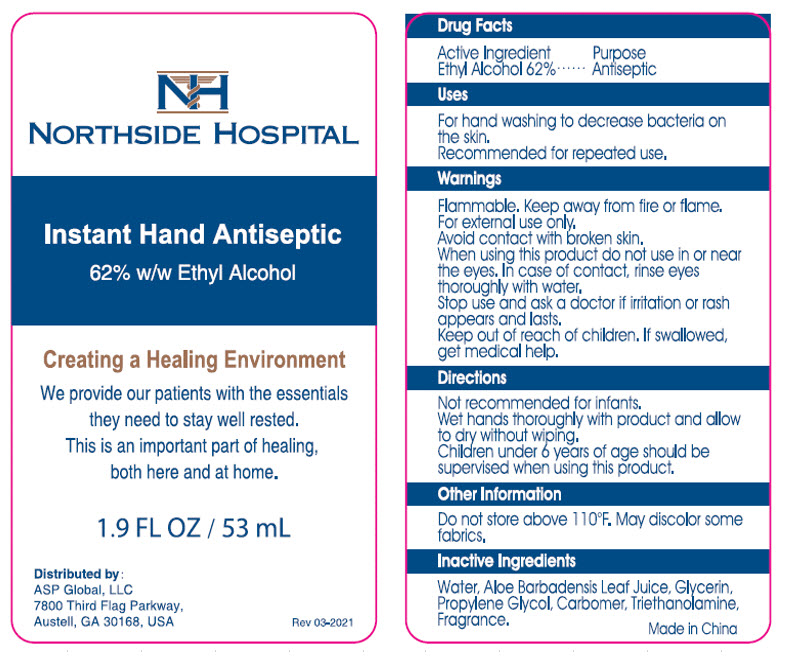 DRUG LABEL: Instant Hand Antiseptic
NDC: 59448-001 | Form: GEL
Manufacturer: ASP Global
Category: otc | Type: HUMAN OTC DRUG LABEL
Date: 20241203

ACTIVE INGREDIENTS: ALCOHOL 62 mL/100 mL
INACTIVE INGREDIENTS: WATER; ALOE VERA LEAF; GLYCERIN; PROPYLENE GLYCOL; CARBOMER INTERPOLYMER TYPE A (ALLYL SUCROSE CROSSLINKED); TROLAMINE

Active Ingredient:
Ethyl Alcohol 62%

Purpose Antiseptic

Warnings: Flammable. Keep away from fire or flame.

For external use only.

Avoid contact with broken skin.

Stop use and ask a doctor if irritation or rash appears and lasts.

Keep out of reach of children. If swallowed, get medical help.

Directions:

Not recommended for infants.

Wet hands thoroughly with product and allow to dry without wiping.

Children under 6 years of age must be supervised when using this product.

INACTIVE INGREDIENT

Inactive Ingredients: Water, Glycerin, Propylene glycol, Carbomer, Triethanolamine,Aloe Barbadensis Leaf Juice,

Other Information:

Do not store above 110 F. May discolor some fabrics.

INDICATIONS AND USAGE

Uses: For hand washing to decrease bacteria on the skin. Recommended for repeated use.

When using this product do not use in or near the eyes. In case of contact, rinse eyes thoroughly with water.

PRINCIPAL DISPLAY PANEL - 53 mL Bottle Label

NORTHSIDE HOSPITAL

Instant Hand Antiseptic
62% w/w Ethyl Alcohol

Creating a Healing Environment

We provide our patients with the essentials
they need to stay well rested.
This is an important part of healing,
both here and at home.

1.9 FL OZ / 53 mL

Distributed by:
ASP Global, LLC
7800 Third Flag Parkway,
Austell, GA 30168, USA

Rev 03-2021